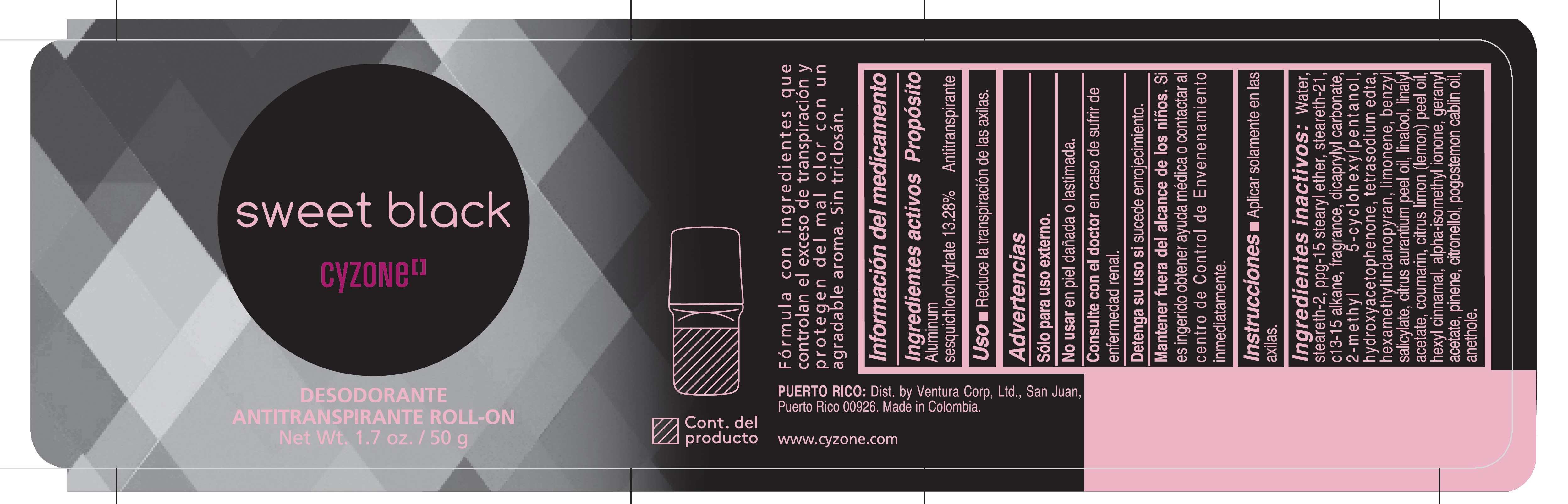 DRUG LABEL: CYZONE SWEET BLACK DESODORANTE ANTITRANSPIRANTE ROLL ON
NDC: 14141-459 | Form: EMULSION
Manufacturer: BEL STAR SA
Category: otc | Type: HUMAN OTC DRUG LABEL
Date: 20251202

ACTIVE INGREDIENTS: ALUMINUM SESQUICHLOROHYDRATE 132.8 mg/1 g
INACTIVE INGREDIENTS: LINALOOL; STEARETH-2; TETRASODIUM EDTA; CITRUS LIMON (LEMON) PEEL OIL; GERANYL ACETATE; LIMONENE, (+)-; HEXAMETHYLINDANOPYRAN; STEARETH-21; 2-METHYL 5-CYCLOHEXYLPENTANOL; COUMARIN; HYDROXYACETOPHENONE; BENZYL SALICYLATE; POGOSTEMON CABLIN OIL; WATER; PPG-15 STEARYL ETHER; C13-15 ALKANE; ANETHOLE; CITRUS AURANTIUM PEEL OIL; CITRONELLOL; ALPHA-ISOMETHYL IONONE; PINENE; LINALYL ACETATE; HEXYL CINNAMAL; DICAPRYLYL CARBONATE

CYZONE SWEET BLACK DESODORANTE ANTITRANSPIRANTE ROLL ON

Ingredientes activos

Aluminum sesquichlorohydrate 13.28%

Proposito

Antitranspirante

Uso

- Reduce la transpiracion de las axilas.

Advertencias

Solo para uso externo.

No usar

en piel danada o lastimada.

Consulte con el doctor

en caso de sufrir de enfermedad renal.

Detenga su uso si

sucede enrojecimiento.

Mantener fuera del alcance de los ninos.

Si es ingerido obtener ayuda medica o contactar al centro de Control de Envenenamiento inmediatamente.

Instrucciones

- Aplicar solamente en las axilas.

Ingredientes inactivos

water, steareth-2, ppg-15 stearyl ether, steareth-21, c13-15 alkane, fragrance, dicaprylyl carbonate, 2-methyl 5-cyclohexylpentanol, hydroxyacetophenone, tetrasodium edta, hexamethylindanopyran, limonene, benzyl salicylate, citrus aurantium peel oil, linalool, linalyl acetate, coumarin, citrus limon (lemon) peel oil, hexyl cinnamal, alpha-isomethyl ionone, geranyl acetate, pinene, citronellol, pogostemon cablin oil, anethole.